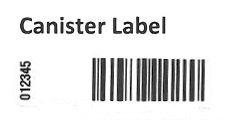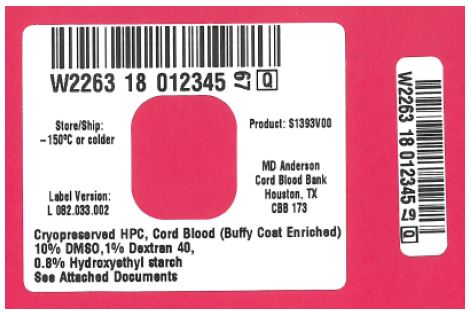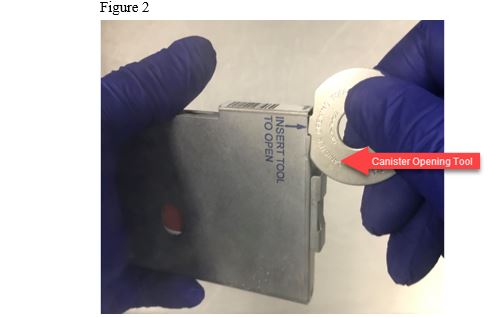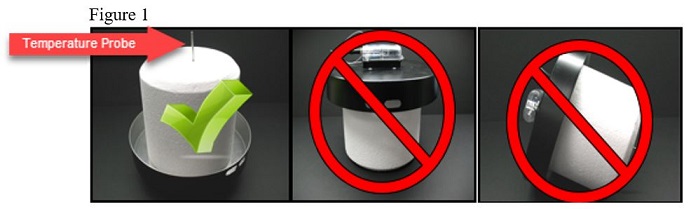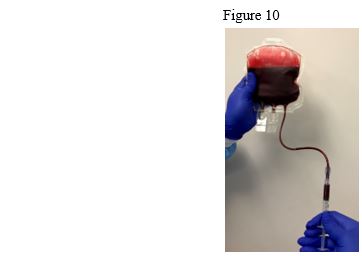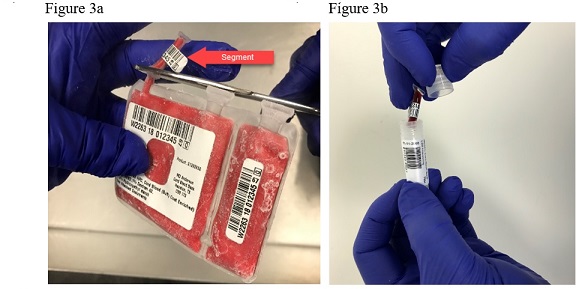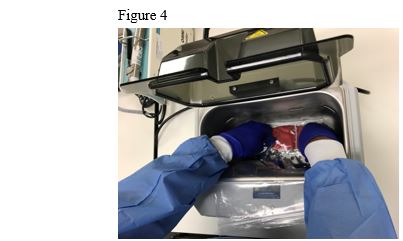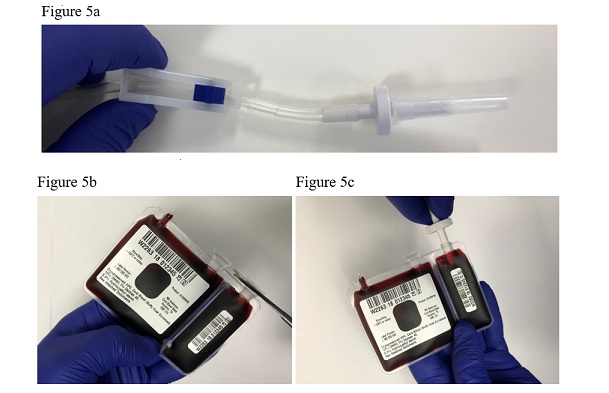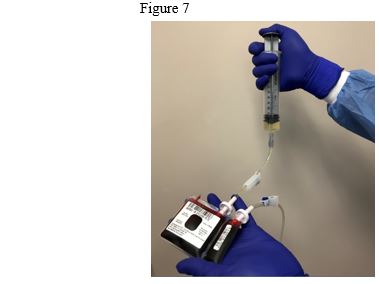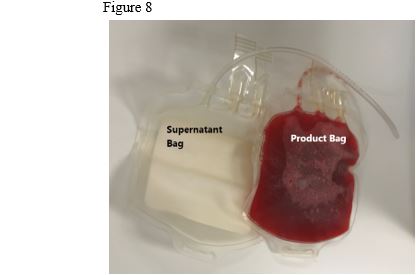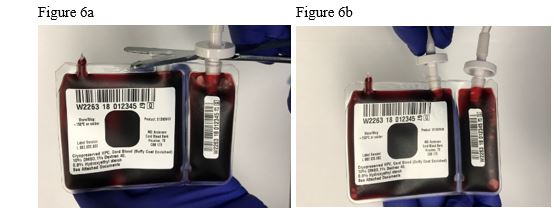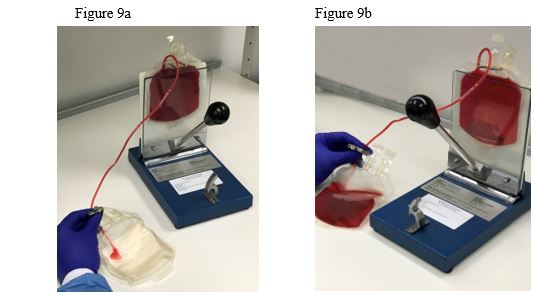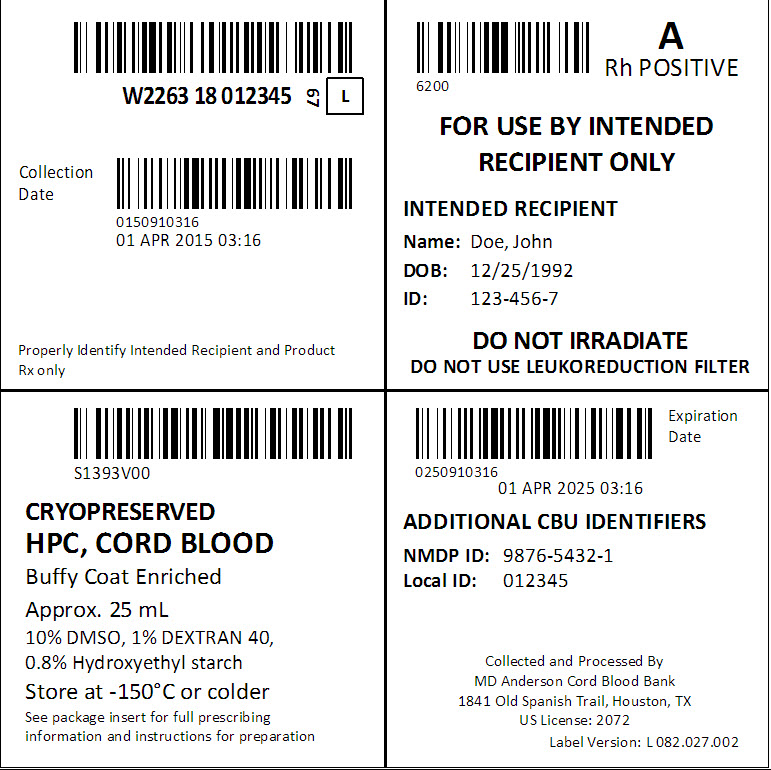 DRUG LABEL: HEMATOPOIETIC PROGENITOR CELLS, CORD BLOOD
NDC: W2263-S1393 | Form: SOLUTION
Manufacturer: University of Texas MD Anderson Cancer Center
Category: other | Type: LICENSED MINIMALLY MANIPULATED CELLS LABEL
Date: 20180626

ACTIVE INGREDIENTS: Human Cord Blood Hematopoietic Progenitor Cell 900000000 1/25 mL
INACTIVE INGREDIENTS: Dextran 40; Dimethyl Sulfoxide

HIGHLIGHTS OF PRESCRIBING INFORMATION

These highlights do not include all the information needed to use HPC, Cord Blood safely and effectively. See full prescribing information for HPC, Cord Blood.
HPC, Cord Blood
Injectable Suspension for Intravenous Use
Initial U.S. Approval: 2018

WARNING: FATAL INFUSION REACTIONS, GRAFT VERSUS HOST DISEASE, ENGRAFTMENT SYNDROME, AND GRAFT FAILURE

See full prescribing information for complete boxed warning.

- Fatal infusion reactions: Monitor patients during infusion and discontinue for severe reactions. (5.1, 5.2)
- Graft-versus-Host disease (GVHD): GVHD may be fatal. Administration of immunosuppressive therapy may decrease the risk of GVHD. (5.3)
- Engraftment syndrome: Engraftment syndrome may be fatal. Treat engraftment syndrome promptly with corticosteroids. (5.4)
- Graft failure: Graft failure may be fatal. Monitor patients for laboratory evidence of hematopoietic recovery. (5.5)

1 INDICATIONS AND USAGE

Hematopoietic Progenitor Cell (HPC), Cord Blood, is an allogeneic cord blood hematopoietic progenitor cell therapy indicated for use in unrelated donor hematopoietic progenitor cell transplantation procedures in conjunction with an appropriate preparative regimen for hematopoietic and immunologic reconstitution in patients with disorders affecting the hematopoietic system that are inherited, acquired, or result from myeloablative treatment. (1)

The benefit-risk assessment for an individual patient depends on the patient characteristics, including disease, stage, risk factors, and specific manifestations of the disease, on characteristics of the graft, and on other available treatments or types of hematopoietic progenitor cells. (1)

2 DOSAGE AND ADMINISTRATION

- For intravenous use only.
- Do not irradiate.
- Unit selection and administration of HPC, Cord Blood should be done under the direction of a physician experienced in hematopoietic progenitor cell transplantation. (2)
- The recommended minimum dose is 2.5 x 10^7 nucleated cells/kg at cryopreservation. (2.1)
- Do not administer HPC, Cord Blood through the same tubing with other products except for normal saline. (2.3)

3 DOSAGE FORMS AND STRENGTHS

Each unit contains a minimum of 9 x 10^8 total nucleated cells with at least 1.25 x 10^6 viable CD34+ cells at the time of cryopreservation. The exact pre- cryopreservation nucleated cell content of each unit is provided on the container label and accompanying records. (3)

4 CONTRAINDICATIONS

None. (4)

5 WARNINGS AND PRECAUTIONS

- Hypersensitivity Reactions (5.1)
- Infusion Reactions (5.2)
- Graft-versus-Host Disease (5.3)
- Engraftment Syndrome (5.4)
- Graft Failure (5.5)
- Malignancies of Donor Origin (5.6)
- Transmission of Serious Infections (5.7)
- Transmission of Rare Genetic Diseases (5.8)

6 ADVERSE REACTIONS

Mortality, from all causes, at 100 days post-transplant was 25%. (5, 6.1)

The most common infusion-related adverse reactions (≥5%) are hypertension, vomiting, nausea, bradycardia, and fever. (6.1)

To report SUSPECTED ADVERSE REACTIONS, contact the MD Anderson Cord Blood Bank, The University of Texas MD Anderson Cancer Center, at 1-713-563-8000 and FDA at 1-800-FDA-1088 or https://www.fda.gov/Safety/MedWatch.

8 USE IN SPECIFIC POPULATIONS

- Pregnancy: Based on animal data, may cause fetal harm. Use only if clearly needed. (8.1)

FULL PRESCRIBING INFORMATION

WARNING: FATAL INFUSION REACTIONS, GRAFT VERSUS HOST DISEASE, ENGRAFTMENT SYNDROME, AND GRAFT FAILURE

Fatal infusion reactions: HPC, Cord Blood administration can result in serious, including fatal, infusion reactions. Monitor patients and discontinue HPC, Cord Blood infusion for severe reactions. [See Warnings and Precautions (5.1, 5.2)]

Graft-versus-Host disease (GVHD): GVHD is expected after administration of HPC, Cord Blood, and may be fatal. Administration of immunosuppressive therapy may decrease the risk of GVHD. [See Warnings and Precautions (5.3)]

Engraftment syndrome: Engraftment syndrome may progress to multi-organ failure and death. Treat engraftment syndrome promptly with corticosteroids. [See Warnings and Precautions (5.4)]

Graft failure: Graft failure may be fatal. Monitor patients for laboratory evidence of hematopoietic recovery. Prior to choosing a specific unit of HPC, Cord Blood, consider testing for HLA antibodies to identify patients who are alloimmunized. [See Warnings and Precautions (5.5)]

1 INDICATIONS AND USAGE

Hematopoietic Progenitor Cell (HPC), Cord Blood, is an allogeneic cord blood hematopoietic progenitor cell therapy indicated for use in unrelated donor hematopoietic progenitor stem cell transplantation procedures in conjunction with an appropriate preparative regimen for hematopoietic and immunologic reconstitution in patients with disorders affecting the hematopoietic system that are inherited, acquired, or result from myeloablative treatment.

The benefit-risk assessment for an individual patient depends on the patient characteristics, including disease, stage, risk factors, and specific manifestations of the disease, on characteristics of the graft, and on other available treatments or types of hematopoietic progenitor cells.

2 DOSAGE AND ADMINISTRATION

For intravenous use only.
Do not irradiate.

Unit selection and administration of HPC, Cord Blood should be done under the direction of a physician experienced in hematopoietic progenitor cell transplantation.

2.1 Dosing

The recommended minimum dose is 2.5 x 10^7 total nucleated cells/kg at cryopreservation. Multiple units may be required in order to achieve the appropriate dose.

Matching for at least 4 of 6 HLA-A antigens, HLA-B antigens, and HLA-DRB1 alleles is recommended. The HLA typing and nucleated cell content for each individual unit of HPC, Cord Blood are documented on the container label and/or in accompanying records.

2.2 Preparation for Infusion

HPC, Cord Blood should be prepared by a trained healthcare professional.

- Do not irradiate HPC, Cord Blood.
- See the appended detailed instructions for preparation of HPC, Cord Blood for infusion.
- Once prepared for infusion, HPC, Cord Blood may be stored at 4 to 8 °C for up to 30 minutes if product is thawed and DMSO is not removed, or at 4 to 8 °C for up to 4 hours if DMSO is removed in a washing procedure [see Instructions for Preparation for Infusion]. No data are available for the stability of HPC, Cord Blood if DMSO is not removed.
- The recommended limit on DMSO administration is 1 gram per kg body weight per day. [See Warnings and Precautions (5.2) and Overdosage (10)]

2.3 Administration

HPC, Cord Blood should be administered under the supervision of a qualified healthcare professional experienced in hematopoietic progenitor cell transplantation.

1. Confirm the identity of the patient for the specified unit of HPC, Cord Blood prior to administration.
2. Confirm that emergency medications are available for use in the immediate area.
3. Ensure the patient is hydrated adequately.
4. Premedicate the patient 30 to 60 minutes before the administration of HPC, Cord Blood. Premedication can include all of the following: antipyretics, histamine antagonists, and corticosteroids.
5. Inspect the product for any abnormalities, such as particulates, and for breaches of container integrity prior to administration. Prior to infusion, discuss all such product irregularities with the laboratory issuing the product for infusion.
6. Administer HPC, Cord Blood by intravenous infusion. Do not administer in the same tubing concurrently with products other than 0.9% Sodium Chloride, Injection (USP). HPC, Cord Blood may be filtered through a 170 to 260 micron filter designed to remove clots. Do NOT use a filter designed to remove leukocytes.
7. For adults, begin infusion of HPC, Cord Blood at 100 milliliters per hour and increase the rate as tolerated.
  For children, begin infusion of HPC, Cord Blood at 1 milliliter per kg per hour and increase as tolerated.
  Reduce the infusion rate if the fluid load is not tolerated. Discontinue the infusion in the event of an allergic reaction or if the patient develops a moderate to severe infusion reaction. [See Warnings and Precautions (5.2) and Adverse Reactions (6)]
8. Monitor the patient for adverse reactions during, and for at least six hours after, administration. Because HPC, Cord Blood contains lysed red cells that may cause renal failure, careful monitoring of urine output is also recommended.

NOTE: If product is being prepared for a multi-unit infusion, infuse units independently. Should a reaction occur, appropriately manage the reaction before the second unit is thawed for infusion.

3 DOSAGE FORMS AND STRENGTHS

Each unit of HPC, Cord Blood contains a minimum of 9.0 x 10^8 total nucleated cells with a minimum of 1.25 x 10^6 viable CD34+ cells, suspended in 10% dimethyl sulfoxide (DMSO) and 1% Dextran 40, at the time of cryopreservation.

The exact pre-cryopreservation nucleated cell content is provided on the container label and in accompanying records.

4 CONTRAINDICATIONS

None.

5 WARNINGS AND PRECAUTIONS

5.1 Hypersensitivity Reactions

Allergic reactions may occur with infusion of HPC, Cord Blood including HPC, Cord Blood manufactured by MD Anderson Cord Blood Bank. Reactions include bronchospasm, wheezing, angioedema, pruritus, and hives [see Adverse Reactions (6.1)]. Serious hypersensitivity reactions, including anaphylaxis, also have been reported. These reactions may be due to dimethyl sulfoxide (DMSO), Dextran 40, hydroxyethyl starch, or a plasma component of HPC, Cord Blood.

HPC, Cord Blood may contain residual antibiotics if the cord blood donor was exposed to antibiotics in utero. Patients with a history of allergic reactions to antibiotics should be monitored for allergic reactions following HPC, Cord Blood administration.

5.2 Infusion Reactions

Infusion reactions are expected to occur and may include nausea, vomiting, fever, rigors or chills, flushing, dyspnea, hypoxemia, chest tightness, hypertension, tachycardia, bradycardia, dysgeusia, hematuria, and mild headache. Premedication with antipyretics, histamine antagonists, and corticosteroids may reduce the incidence and intensity of infusion reactions.

Severe reactions, including respiratory distress, severe bronchospasm, severe bradycardia with heart block or other arrhythmias, cardiac arrest, hypotension, hemolysis, elevated liver enzymes, renal compromise, encephalopathy, loss of consciousness, and seizure also may occur. Many of these reactions are related to the amount of DMSO administered. Minimizing the amount of DMSO administered may reduce the risk of such reactions, although idiosyncratic responses may occur even at DMSO doses thought to be tolerated. The actual amount of DMSO depends on the method of preparation of the product for infusion. Limiting the amount of DMSO infused to no more than 1 gram per kilogram per day is recommended. [See Overdosage (10)]

Infusion reactions may begin within minutes of the start of infusion of HPC, Cord Blood, although symptoms may continue to intensify and not peak for several hours after completion of the infusion. Monitor the patient closely during this period. When a reaction occurs, discontinue the infusion and institute supportive care as needed. If infusing more than one unit of HPC, Cord Blood on the same day, do not administer subsequent units until all signs and symptoms of infusion reactions from the prior unit have resolved.

5.3 Graft-versus-Host Disease

Acute and chronic graft-versus-host disease (GVHD) may occur in patients who have received HPC, Cord Blood. Classic acute GVHD is manifested as fever, rash, elevated bilirubin and liver enzymes, and diarrhea. Patients transplanted with HPC, Cord Blood should receive immunosuppressive drugs to decrease the risk of GVHD. [See Adverse Reactions (6.1)]

5.4 Engraftment Syndrome

Engraftment syndrome is manifested as unexplained fever and rash in the peri-engraftment period. Patients with engraftment syndrome also may have unexplained weight gain, hypoxemia, and pulmonary infiltrates in the absence of fluid overload or cardiac disease. If untreated, engraftment syndrome may progress to multi-organ failure and death. Once engraftment syndrome is recognized, begin treatment with corticosteroids in order to ameliorate the symptoms. [See Adverse Reactions (6.1)]

5.5 Graft Failure

Primary graft failure, which may be fatal, is defined as failure to achieve an absolute neutrophil count greater than 500 cells per microliter of blood by Day 42 after transplantation. Immunologic rejection is the primary cause of graft failure. Patients should be monitored for laboratory evidence of hematopoietic recovery. Consider testing for HLA antibodies in order to identify patients who are alloimmunized prior to transplantation and to assist with choosing a unit with a suitable HLA type for the individual patient. [See Adverse Reactions (6.1)]

5.6 Malignancies of Donor Origin

Patients who have undergone HPC, Cord Blood transplantation may develop post-transplant lymphoproliferative disorder (PTLD), manifested as a lymphoma-like disease favoring non-nodal sites. PTLD is usually fatal if not treated.

The incidence of PTLD appears to be higher in patients who have received antithymocyte globulin. The etiology is thought to be donor lymphoid cells transformed by Epstein-Barr virus (EBV). Serial monitoring of blood for EBV DNA may be warranted in high-risk groups.

Leukemia of donor origin also has been reported in HPC, Cord Blood recipients. The natural history is presumed to be the same as that for de novo leukemia.

5.7 Transmission of Serious Infections

Transmission of infectious disease may occur because HPC, Cord Blood is derived from human blood. Disease may be caused by known or unknown infectious agents. Donors are screened for increased risk of infection with human immunodeficiency virus (HIV), human T-cell lymphotropic virus (HTLV), hepatitis B virus (HBV), hepatitis C virus (HCV), T. pallidum, T. cruzi, West Nile virus (WNV), transmissible spongiform encephalopathy (TSE) agents, vaccinia and Zika virus. Donors are also screened for clinical evidence of sepsis, and communicable disease risks associated with xenotransplantation. Maternal blood samples are tested for HIV types 1, 2 and O, HTLV types I and II, HBV, HCV, T. pallidum, WNV, and T. cruzi. HPC, Cord Blood is tested for sterility. These measures do not completely eliminate the risk of transmitting these or other transmissible infectious diseases and disease agents. Report the occurrence of a transmitted infection to MD Anderson Cord Blood Bank, The University of Texas MD Anderson Cancer Center at 1-713-563-8000.

Testing of maternal blood is also performed for evidence of donor infection due to cytomegalovirus (CMV).

Test results may be found on the container label and/or in accompanying records.

5.8 Transmission of Rare Genetic Diseases

HPC, Cord Blood may transmit rare genetic diseases involving the hematopoietic system for which donor screening and/or testing has not been performed [see Adverse Reactions (6.1)]. Cord blood donors have been screened by family history to exclude inherited disorders of the blood and marrow. HPC, Cord Blood has been tested to exclude donors with sickle cell anemia, and anemias due to abnormalities in hemoglobins C, D, and E. Because of the age of the donor at the time HPC, Cord Blood collection takes place, the ability to exclude rare genetic diseases is severely limited.

6 ADVERSE REACTIONS

Day-100 mortality from all causes was 25%.

The most common infusion-related adverse reactions (≥ 5%) are hypertension, vomiting, nausea, bradycardia, and fever.

6.1 Clinical Trials Experience

Because clinical trials are conducted under widely varying conditions, adverse reaction rates observed in the clinical trials of a drug cannot be directly compared to rates in the clinical trials of another drug and may not reflect the rates observed in practice.

The safety assessment of HPC, Cord Blood is based primarily on review of the data submitted to the FDA dockets from various sources, the dataset for the COBLT^1 Study, and published literature.

Infusion Reactions

The Cord Blood Transplantation study group conducted a prospective study (COBLT^1) of unrelated cord blood transplantation (CBT) to better define the role of this stem cell source for subjects requiring unrelated allogeneic transplantation. The primary end point of the study was survival at 180 days. Secondary end points included engraftment, graft-versus-host disease, relapse, and long-term survival. Eligibility criteria for malignant and nonmalignant diseases were specified.

The data described in Table 1 reflect exposure to 442 infusions of HPC, Cord Blood (from multiple cord blood banks) in patients treated using a total nucleated cell dose ≥ 2.5 x 10^7/kg on a single-arm trial or expanded access use (The COBLT^1 Study). The population was 60% male, the median age was 5 years (range 0.05-68 years), and included patients treated for hematologic malignancies, inherited metabolic disorders, primary immunodeficiencies, and bone marrow failure. Preparative regimens and GVHD prophylaxis were not standardized. The most common infusion reactions were hypertension, vomiting, nausea, and sinus bradycardia. Hypertension and grades 3-4 infusion-related reactions occurred more frequently in patients receiving HPC, Cord Blood in volumes greater than 150 milliliters and in pediatric patients. The rate of serious adverse cardiopulmonary reactions was 0.8%.

Table 1. Incidence of Infusion-Related Adverse Reactions Occurring in ≥1% of Infusions (The COBLT^1 Study)
 | Any grade | Grade 3-4
Any reaction | 65.4% | 27.6%
Hypertension | 48.0% | 21.3%
Vomiting | 14.5% | 0.2%
Nausea | 12.7% | 5.7%
Sinus bradycardia | 10.4% | 0
Fever | 5.2% | 0.2%
Sinus tachycardia | 4.5% | 0.2%
Allergy | 3.4% | 0.2%
Hypotension | 2.5% | 0
Hemogloburia | 2.1% | 0
Hypoxia | 2.0% | 2.0%

Information on infusion reactions was available from voluntary reports for 846 patients who received cord blood units manufactured at MD Anderson Cord Blood Bank with a TNC dose ≥ 2.5 x 10^7/kg and HLA match grade ≥ 4/6. The population included 59% males and 41% females with median age of 25 years (range 0.1-73 years). Preparative regimens and GVHD prophylaxis were not standardized. The reactions, as reported to the MD Anderson Cord Blood Bank by the Stem Cell Outcomes Database (SCTOD) of the Center for International Blood and Marrow Transplant Research (CIBMTR), were not graded. Twenty-two percent of infusions (n=187) were associated with an infusion reaction. The most common infusion reactions, occurring in >1% of infusions, were hypertension (17.1%), nausea (4.3%), vomiting (3.9%), and headache (1.2%).

Other Adverse Reactions

For other adverse reactions, the raw clinical data from the docket were pooled for 1299 (120 adult and 1179 pediatric) patients transplanted with HPC, Cord Blood (from multiple cord blood banks) with total nucleated cell dose ≥2.5 x 10^7/kg. Sixty-six percent (n=862) underwent transplantation as treatment for hematologic malignancy. The preparative regimens and GVHD prophylaxis varied. The median total nucleated cell dose was 6.4 x 10^7/kg (range 2.5-73.8 10^7/kg). For these patients, Day-100 mortality from all causes was 25%. Primary graft failure occurred in 16%; 42% developed grades 2-4 acute GVHD and 19% developed grades 3-4 acute GVHD.

Data from published literature and from observational registries, institutional databases, and cord blood bank reviews reported to the docket for HPC, Cord Blood (from multiple cord blood banks) revealed nine cases of donor cell leukemia, one case of transmission of infection, and one report of transplantation from a donor with an inheritable genetic disorder. The data are not sufficient to support reliable estimates of the incidences of these events.

In the COBLT^1 study, 15% of the patients developed engraftment syndrome.

8 USE IN SPECIFIC POPULATIONS

8.1 Pregnancy

Risk Summary

There are no data with HPC, Cord Blood use in pregnant women to inform a product-associated risk. Animal reproduction studies have not been conducted with HPC, Cord Blood. In the U.S. general population, the estimated background risk of major birth defects and miscarriage in clinically recognized pregnancies is 2-4% and 15-20%, respectively.

8.2 Lactation

Risk Summary

There is no information regarding the presence of HPC, Cord Blood in human milk, the effects on the breastfed infant, or the effects on milk production. The developmental and health benefits of breastfeeding should be considered along with the mother's clinical need for HPC, Cord Blood and any potential adverse effects on the breastfed infant from HPC, Cord Blood or from the underlying maternal condition.

8.4 Pediatric Use

HPC, Cord Blood has been used in pediatric patients with disorders affecting the hematopoietic system that are inherited, acquired, or resulted from myeloablative treatment. [See Dosage and Administration (2), Adverse Reactions (6), and Clinical Studies (14)]

8.5 Geriatric Use

Clinical studies of HPC, Cord Blood (from multiple cord blood banks) did not include sufficient numbers of subjects aged 65 and over to determine whether they respond differently than younger subjects. In general, administration of HPC, Cord Blood to patients over age 65 should be cautious, reflecting their greater frequency of decreased hepatic, renal, or cardiac function, and of concomitant disease or other drug therapy.

8.6 Renal Disease

HPC, Cord Blood contains Dextran 40, which is eliminated by the kidneys. The safety of HPC, Cord Blood has not been established in patients with renal insufficiency or renal failure.

10 OVERDOSAGE

10.1 Human Overdosage Experience

There has been no experience with overdose of HPC, Cord Blood in human clinical trials. Single doses of HPC, Cord Blood up to 5.0 x 10^8 TNC/kg have been administered. HPC, Cord Blood prepared for infusion may contain dimethyl sulfoxide (DMSO). The maximum tolerated dose of DMSO has not been established, but it is customary not to exceed a DMSO dose of 1 gm/kg/day when given intravenously. Several cases of altered mental status and coma have been reported with higher doses of DMSO.

10.2 Management of Overdose

For DMSO overdose, general supportive care is indicated. The role of other interventions to treat DMSO overdose has not been established.

11 DESCRIPTION

HPC, Cord Blood consists of hematopoietic progenitor cells, monocytes, lymphocytes, and granulocytes from human cord blood for intravenous infusion. Blood recovered from the umbilical cord and placenta is volume reduced and partially depleted of red blood cells and plasma.

The active ingredient is hematopoietic progenitor cells, which express the cell surface marker CD34. The potency of cord blood is determined by measuring the numbers of total nucleated cells (TNC) and CD34+ cells, and cell viability. Each unit of HPC, Cord Blood contains a minimum of 9.0 x 10^8 total nucleated cells with at least 1.25 x 10^6 viable CD34+ cells at the time of cryopreservation. The cellular composition of HPC, Cord Blood depends on the composition of cells in the blood recovered from the umbilical cord and placenta of the donor. The actual nucleated cell count, the CD34+ cell count, the ABO group, and the human leukocyte antigen (HLA) typing are listed on the container label and/or accompanying records sent with each individual unit.

HPC, Cord Blood has the following inactive ingredients: dimethyl sulfoxide (DMSO), citrate phosphate dextrose (CPD), hydroxyethyl starch, and Dextran 40. When prepared for infusion according to instructions, the infusate contains the following inactive ingredients: Dextran 40, human serum albumin, residual DMSO, residual hydroxyethyl starch and residual CPD.

12 CLINICAL PHARMACOLOGY

12.1 Mechanism of Action

Hematopoietic stem/progenitor cells from HPC, Cord Blood migrate to the bone marrow where they divide and mature. The mature cells are released into the bloodstream, where some circulate and others migrate to tissue sites, partially or fully restoring peripheral blood counts and function, including immune function, of blood-borne cells of marrow origin. [See Clinical Studies (14)]

In patients with enzymatic abnormalities due to certain severe types of storage disorders, mature leukocytes resulting from HPC, Cord Blood transplantation may synthesize enzymes that may be able to circulate and improve cellular functions of some native tissues. However, the precise mechanism of action is unknown.

14 CLINICAL STUDIES

The effectiveness of HPC, Cord Blood, as defined by hematopoietic reconstitution, was demonstrated in the single-arm prospective COBLT^1 study, and in retrospective review of data from an observational database for MD Anderson Cord Blood Bank, using data from the Center for International Blood and Marrow Transplant Research (CIBMTR), the National Marrow Donor Program (NMDP), and data in the FDA dockets and public information. The total nucleated cell dose and degree of HLA match were inversely associated with the time to neutrophil recovery in the docket data. Sixty-six percent (n=862) of the 1299 patients in the docket and public data underwent transplantation as treatment for hematologic malignancy. In the MD Anderson Cord Blood Bank database, 84% of patients (708 of 846) underwent transplantation for a hematologic malignancy.

Table 2 describes the recipient characteristics and hematopoietic recovery of 846 patients who received a total nucleated cell dose of ≥ 2.5 x 10^7/kg from at least a single cord blood unit manufactured at MD Anderson Cord Blood Bank, alone or in combination with another unit of HPC, Cord Blood and who had an HLA match ≥ 4/6, as well as the outcomes from the COBLT^1 study and the docket data.

Neutrophil recovery is defined as the time from transplantation to an absolute neutrophil count greater than 500 cells/μL. Platelet recovery is the time to a platelet count greater than 20,000 cells/μL without a platelet transfusion for the preceding seven days. Erythrocyte recovery is the time to a reticulocyte count greater than 30,000 cells/μL.

Table 2: Hematopoietic Recovery in Patients Transplanted with HPC, Cord Blood units supplied by the MD Anderson Cord Blood Bank compared to the COBLT^1 study and Docket Data
Data Source | The COBLT^1 Study | Docket and Public Data | MD Anderson Cord Blood Bank Data*
Design | Single-arm prospective | Retrospective | Retrospective
Number of patients | 324 | 1299 | 846
Median age (range) years | 4.6 (0.07 - 52.2) | 7.0 (&lt;1 - 65.7) | 24.8 (0.1 – 73.3)
Sex | 59% male | 57% male | 58% male
Sex | 41% female | 43% female | 42% female
Median Weight (range) at transplant (kg) | NA | NA | 59 (2.6-146.0)
Median TNC Dose (range) (x 10^7/kg) | 6.7 (2.6 -38.8) | 6.4 (2.5- 73.8) | 5.4 (2.5-76.9)
Neutrophil Recovery at Day 42 (ANC &gt; 500/µL) (95% Cl) | 76% (71% - 81%) | 77% (75% - 79%) | 88.2% (85.9% - 90.2%)
Platelet Recovery at Day 100 (20,000/µL) (95% CI) | 57% (51% - 63%) | NA | 73.6% (70%-77%)
Platelet Recovery at Day 100 (50,000/µL) (95% Cl) | 46% (39% - 51%) | 45% (42% - 48%) | 43% (39%, 46%)
Erythrocyte Recovery at Day 100 (95% CI) | 65% (58%-7 1%) | NA | NA
Median Time to Neutrophil Recovery | 27 days | 25 days | 19 days
Median Time to Platelet Recovery (20,000/µL) | 90 days | NA | 47 days
Median Time to Platelet Recovery (20,000/µL) | 113 days | 122 days | 65 days
Median Days to Erythrocyte Recovery | 64 days | NA | NA
*Data from patients who received a suitable allograft (TNC ≥ 2.5 x 10^7/kg and ≥ 4/6 HLA match). Note that evaluable data for outcomes were not available for all patients and there are various amounts of missing data. NA: Not Available

15 REFERENCES

1. Cornetta K, Laughlin M, Carter S, et al. Umbilical cord blood transplantation in adults: results of the prospective Cord Blood Transplantation (COBLT). Biol Blood Marrow Transplant 2005;11:149-60.

16 HOW SUPPLIED/STORAGE AND HANDLING

HPC, Cord Blood is supplied as a cryopreserved cell suspension in a sealed bag containing a minimum of 9.0 x 10^8 total nucleated cells with a minimum of 1.25 x 10^6 viable CD34+ cells in a volume of 25 milliliters (ISBT 128 Product Code S1393, ISBT 128 Facility Identifier Number W2263). The exact pre-cryopreservation nucleated cell content is provided on the container label and accompanying records.

Store HPC, Cord Blood at or below -150°C until ready for thawing and preparation.

17 PATIENT COUNSELING INFORMATION

Discuss the following with patients receiving HPC, Cord Blood:

- Report immediately any signs and symptoms of acute infusion reactions, such as fever, chills, fatigue, breathing problems, dizziness, nausea, vomiting, headache, or muscle aches.
- Report immediately any signs or symptoms suggestive of graft-vs-host disease, including rash, diarrhea, or yellowing of the eyes.

INSTRUCTIONS FOR PREPARATION FOR INFUSION

MD Anderson Cord Blood Bank recommends washing of the HPC, Cord Blood unit prior to infusion. Once the wash procedure is complete, the product must be infused within four hours. Included below are instructions for washing HPC, Cord Blood. Prior to thawing of the unit, read the thaw and wash instructions and emergency product recovery procedure below. Prepare all required reagents, supplies, equipment, and forms listed, and ensure they are readily available.

1 Reagents

- Human serum albumin, 5%, USP
- Dextran 40 in Sodium Chloride Injection, USP (10% Low Molecular Weight Dextran in 0.9% Sodium Chloride Injection)
- Sterile water
- 70% Isopropyl Alcohol (for cleaning)

2 Supplies

- Bacterial culture bottles, aerobic and anaerobic [or other supplies for performing sterility testing]
- Bag spike with tubing (2)
- 300 ml transfer pack (2)
- 60 ml sterile disposable syringe with tubing (4)
- 10 ml sterile disposable syringe (2)
- 3 ml sterile disposable syringe with tubing (1)
- 16-gauge needles
- Blunt end needle (Emergency Product Recovery)
- 2 ml cryogenic vial
- Tubes for cell counts, progenitor assays (optional)
- Alcohol prep pads
- Sterile plastic zip-lock bags
- Product labels
- Refrigerated gel/ice pack
- Hemostat or Hoffman clamp
- Absorbent wipes
- Canister opening tool
- Scissors
- Personal protective equipment: gloves
  protective cryogloves
  safety goggles or face shield

3 Equipment

- Biosafety Cabinet
- Liquid nitrogen freezer
- Refrigerated centrifuge
- Water bath
- Sterile tubing connecting device
- Tube sealer, compatible with polyvinyl chloride (PVC)
- Automated cell counter

4 Forms

- Cell Product Shipment Integrity Form
- National Marrow Donor Program (NMDP) Receipt of Cord Blood Unit Form

II PRODUCT RECEIPT AND IDENTITY VERIFICATION

HPC, Cord Blood is shipped frozen at or below -150°C using a liquid nitrogen (LN2) dry shipper. The unit is packed for transport in a stainless steel canister contained within an insulated transport sleeve. Keep HPC, Cord Blood at or below -150°C, either inside the dry shipper container used for shipping or in a liquid nitrogen (LN2) cooled device at the transplant center (recommended). If the HPC, Cord Blood will be stored inside the dry shipper, add liquid nitrogen to the vessel to ensure the unit will be kept at or below -150°C.

Upon receipt of the shipment perform the following steps:

1. Using scissors, cut the zip ties used to secure the outer lid of the liquid nitrogen dry shipper.
2. Open the outer lid of the liquid nitrogen dry shipper and remove shipment documentation packet from inside of lid.
3. Remove the Cell Product Shipment Integrity form from the shipment documentation packet and complete the following information:
  3.1 Record date and time of receipt
  3.2 Inspect shipper for damage or tampering, verify shipper inner lid is secured with tie tag
  3.3 Record temperature from the temperature data logger attached to the inner lid on the
  Cell Product Shipment Integrity form. Check for alarms.
  NOTE: Do not stop the logging process or download data when recording temperature from data logger.
4. Cut the tie tag securing the inner lid assembly and remove inner lid.
  NOTE: The lid assembly should be held by another person or placed, black side down, on a stable surface to protect the temperature probe (see Figure 1).
5. Wearing cryogloves, remove the HPC, Cord Blood product and accompanying samples from the shipper and transfer to vapor phase of liquid nitrogen and maintain temperature at or below -150°C for label and product integrity verification.
  5.1 Remove the canister from the insulated transport sleeve.
  5.2 Remove the canister opening tool from the shipment documentation packet.
  5.3 Using the canister opening tool, carefully pry open the canister at the top and bottom,
  working carefully to avoid damage to the frozen plastic product bag (See Figure 2).
  NOTE: Use of other methods for opening the canister could result in damage to the cryopreserved HPC, Cord Blood product.
6. Verify that the product and any accompanying samples have remained frozen and document
  on the Cell Product Shipment Integrity form.
7. Verify the physical integrity of the cryobag for visible cracks, holes or leaks; document
  cryobag integrity or any damage on the Cell Product Shipment Integrity form.
8. Verify patient/donor name, medical record number and unit number information match the
  information on the bag’s label(s), shipment documentation and your records. Document match
  on the Cell Product Shipment Integrity form.
  NOTE: If there is any error or ambiguity with the HPC, Cord Blood product, accompanying
  samples, or product documentation, keep the product in the canister and store at or
  below -150°C. Report the discrepancy immediately to the MD Anderson Cord Blood
  Bank at 1-713-563-8000. Do not proceed until the problem is resolved.
9. Close the canister and transfer the HPC, Cord Blood cryobag and accompanying samples to
  storage vessels capable of maintaining HPC, Cord Blood at or below -150°C and
  accompanying samples at or below -70°C.
  9.1 If the HPC, Cord Blood cryobag and accompanying samples are to be stored in the dry
  shipper until time of thaw, add additional liquid nitrogen to the dry shipper to ensure the
  product will be maintained at or below -150°C.
  NOTE: Aside from the segment, ancillary samples are not intended to represent the cell
  count or potency of the cryopreserved HPC, Cord Blood product.
10. Fax the completed Cell Product Shipment Integrity form to the MD Anderson Cord Blood
  Bank at 1-713-563-3468.
11. Once use of the dry shipper is complete, prepare for shipment and return to MD Anderson
  Cord Blood bank per instructions provided in the shipment documentation packet.

III PREPARATION

1. General Preparation Information
  1.1. Every attempt should be made to ensure HPC, Cord Blood is thawed rapidly, kept cool after thawing, and
  immediately washed as detailed below in order to limit exposure of thawed cells to DMSO.
  1.2. Use aseptic techniques in a biological safety cabinet (BSC) for processing steps,
  including spiking of the product bag ports and post-wash product sampling.
  1.3 Use only sterile, single use supplies and reagents.
  1.4 Record the manufacturer information, lot number and expiration date (if applicable) of all reagents and
  supplies.
  1.5 Review Section 9: Emergency Product Recovery in the Event of Primary Container
  Failure prior to thawing product. Always thaw the cryobag inside a sterile zip-lock bag
  so product can be recovered if leakage occurs. If product leaks from the cryobag into the
  sterile zip-lock bag, follow the Emergency Product Recovery procedure described below
  in Section 9.
2. Prepare 200 ml Dextran 40/Albumin Wash Solution
  2.1. Aseptically withdraw 100 ml of Human Serum Albumin and 100ml of Dextran 40 and
  combine in a single 300 ml transfer pack (Dextran/Albumin wash solution) labelled with the
  HPC, Cord Blood identifier.
  2.2. Mix contents of the transfer pack.
  NOTE: The transfer bag now contains a total of 200 ml of solution containing both
  Dextran 40 and human serum albumin and will be referred to as the wash solution
  2.3. Using a sterile tubing connecting device, sterile connect a 60ml syringe with tubing to the
  transfer pack containing the Dextran/Albumin wash solution. Withdraw 20 ml of the wash
  solution for diluting the thawed HPC, Cord Blood product.
  2.4. Using a heat sealer, remove the 60ml syringe containing the 20ml aliquot of wash solution
  from the bag of wash solution ensuring to leave enough of the transfer line for additional
  connections.
  2.5. Repeat steps 2.3 through 2.4 to create a second 20ml aliquot of wash solution for rinsing
  the HPC, Cord Blood bag.
  2.6. Using a sterile tubing connecting device, sterile connect a 60ml syringe with tubing to the
  transfer pack containing the Dextran/Albumin wash solution. Withdraw 50 ml of the wash
  solution for resuspending the washed HPC, Cord Blood product/cells.
  2.7 Using a heat sealer, remove the 60ml syringe containing the 50ml aliquot of wash
  solution from the bag of wash solution, ensuring to leave enough of the transfer line for
  connection to the cryobag.
  2.8 Place the transfer pack containing the remaining wash solution and the 60ml syringes into
  a zip-lock bag and store at 2 - 8°C until ready to use.
3. Thawing
  3.1. Fill an empty, clean water bath with sterile water. Verify the set point of water bath is 37±1°C
  3.2. Prior to removal of HPC, Cord Blood from storage, confirm water bath temperature is
  37± 1°C. If the water bath temperature is not within range, wait and/or adjust it such that
  it reaches the desired range.
  3.3. Retrieve canister containing HPC, Cord Blood from storage and place into vapor phase of
  the LN2 freezer or other vessel capable of maintaining temperatures at or below -150°C.
  NOTE: Handle HPC, Cord Blood with extreme caution when removing it from the liquid
  nitrogen, metal cassette and the protective overwrap. Cryobags are very fragile.
  3.4. Working in the vapor phase LN2, remove HPC, Cord Blood cryobag from the metal
  canister.
  3.4.1 Verify label information with a second technologist against transport
  documentation and confirm unit identity and intended recipient.
  NOTE: Labels on HPC, Cord Blood cryobag should match the labels on the
  metal cassette, the tie tag, and on the accompanying paperwork.
  3.4.2 Visually inspect the physical integrity of the cryobag for visible cracks, holes or
  leaks.
  3.5. Using scissors, remove and place the remaining segment in a labeled 2ml cryovial (See
  Figures 3a and 3b). Store the segment in liquid or vapor phase of liquid nitrogen at or
  below -150°C.
  3.6. Gently, wipe the external surface of the cryobag with an absorbent wipe soaked with
  70% isopropyl alcohol.
  3.7. Place the cryobag inside a sterile zip-lock bag, let out the air, and seal the zip-lock bag.
  NOTE: Use of the sterile zip-lock bag allows for recovery of product in the case of an
  unexpected leak or container failure during thawing or centrifugation
  3.8. Place zip-lock bag into 37±1°C water bath.
  3.9. Gently massage the cryobag to promote uniform thawing (See Figure 4). Observe
  cryobag for any sign of leakage.
  3.10. Continue to massage the cryobag until the HPC, Cord Blood reaches a slushy
  consistency. This generally takes about 1-2 minutes.
  3.11. Carefully remove the thawed HPC, Cord Blood cryobag from the zip-lock bag and dry
  off moisture using an absorbent wipe(s).
  3.12 Place the thawed cryobag on ice or cool pack in the BSC.
4. Cell Extraction
  4.1. Using scissors cleaned with an alcohol prep pad, aseptically cut open the port protector
  of the 20% fraction and insert the bag spike with tubing (See Figures 5a, 5b, and 5c).
  NOTE: Ensure clamp on bag spike with tubing is closed prior to spiking bag ports.
  4.2. Using scissors cleaned with alcohol, repeat the process in 4.1 above and aseptically open
  the port protector of the 80% fraction and insert bag spike with tubing (See Figures 6a
  and 6b).
  4.3. With the cryobag on the ice or cool pack, aseptically connect one of the 60ml
  syringes with tubing containing 20 ml of wash solution onto the tubing from the 80% fraction of
  the unit using a sterile connection device.
  4.4. Slowly inject half of the wash media (approx. 10 ml) from the 60ml syringe into the
  HPC, Cord Blood cryobag; gently mix, and then remove the same amount of solution
  added (See Figure 7).
  4.5. Repeat once more by adding half the contents of the 60ml syringe into the HPC, Cord
  Blood cryobag gently mix, and then empty the cryobag compartment by drawing the
  entire contents into the syringe.
  4.6. Using a heat sealer, seal the line attached to the bag spike, ensuring enough tubing is left
  for connection of the second 20ml aliquot of wash solution.
  4.7. Using a sterile tubing connecting device, sterile connect the syringe removed from the
  80% fraction to the 20% fraction and repeat steps 4.5 through 4.8. Seal the line and
  sterile connect the 60ml syringe containing the cells and wash solution to the
  Dextran/Albumin wash transfer pack and add the entire contents of the syringe to the
  300ml transfer pack containing the remainder wash solution; this is now the product
  bag. Mix well.
5. Cryobag Rinse
  5.1. Using a sterile tubing connecting device, sterile connect the second 60ml syringe
  containing 20 ml of wash solution onto the tubing from the 80% fraction of the cryobag.
  5.2. Rinse the 80% compartment with wash solution and collect the contents.
  5.3 Seal the line and remove the syringe.
  5.4 Repeat steps 5.1 through 5.3 for the 20% fraction.
  5.5 Using a sterile tubing connecting device, sterile connect the 60ml syringe containing the
  rinse solution to Dextran/Albumin wash transfer pack and add the entire contents of the
  syringe. Mix well.
  5.6 Clamp the tubing between the syringe and 300ml transfer pack now containing the
  product using a hemostat.
  5.7 Using a sterile tubing connecting device, sterile connect a second 300ml transfer pack to
  the product bag. Do not open weld. This bag will be used to collect the wash
  supernatant (See Figure 8).
6. Centrifugation and Supernatant Removal
  6.1. Place the 300ml transfer pack containing the HPC, Cord Blood product into a sterile zip-lock
  bag supported to sit in the middle of the centrifuge bucket.
  6.2. Balance and centrifuge at 800g for 15 minutes at 4°C.
  6.3. After centrifugation, carefully remove bags from centrifuge bucket ensuring not to
  disturb the cell pellet.
  6.4. Place the bag containing the washed HPC, Cord Blood upright in the plasma expresser.
  6.5. Open the sterile weld to supernatant bag and using a hemostat or Hoffman clamp to
  control flow rate, and carefully express supernatant into the empty transfer pack using
  the plasma expressor until approximately 50 ml remains in the product bag. Carefully
  avoid passage of cells into supernatant (See Figures 9a and 9b).
  6.6. Seal line and remove transfer pack containing supernatant.
  6.7. Resuspend cell pellet in remaining supernatant.
  6.8. Using a sterile tubing connecting device, sterile connect a 60ml syringe with tubing onto
  HPC, Cord Blood product bag and measure the volume.
  6.9. Push the resuspended cells back into the transfer pack.
  6.10. Using a sterile tubing connecting device, sterile connect the 60ml syringe containing 50 ml
  of wash solution to the transfer pack and adjust the volume of the cell suspension in
  the transfer pack to a maximum volume of 100 ml.
  6.11. Record the date/time of completion of the wash procedure.
  6.12. Proceed to Section 7.
7. Preparation of HPC, Cord Blood for Transplantation
  7.1. Using a sterile tubing connecting device, sterile connect a 3ml syringe with tubing to the
  transfer line of the transfer pack containing the washed product (See Figure 10).
  7.2. Working in a BSC, using aseptic technique, aseptically remove a 1 ml sample from the
  washed product using the 3ml syringe with tubing.
  NOTE: Use this sample to perform viability analysis, total nucleated cell count and
  other testing as recommended in Section 8: Quality Control Testing.
  7.3. Using a heat sealer, seal the line between the washed product bag and the 3ml syringe.
  Separate the 3ml syringe from the line by cutting through the seal using scissors.
  7.4. Working in a BSC, using aseptic technique, use two 10ml syringes to
  obtain two separate 8 ml aliquots of wash supernatant from the supernatant transfer pack for
  sterility testing.
  7.5. Calculate viable cell recovery using the following formula:
  (Total Viable Nucleated Cells on the Infusion Ready Product ÷ Total Viable Nucleated
  Cells of Cryopreserved Unit Provided on Shipment Report) x 100%
  7.6 Label the infusion bag with patient and donor information per institutional standard
  operating procedures.
  7.7 Label the infusion bag with the washed product expiration date/time. The expiration
  date/time of the washed product is four hours from completion of wash procedure
  described in Section 6.
  7.8 Confirm and document, with a second technologist or designee, the cord blood identifier
  is affixed to infusion bag.
  7.9 Complete appropriate site-specific laboratory forms to document the thawing process
  and final volumes.
  7.10 Transport infusion bag to the site of administration to the patient in a transport container
  capable of maintaining the unit temperature between 2 - 22°C.
  7.11 Infuse within four hours of completion of wash procedure.
  7.12 Infuse the product through a 170-260 micron filter at the bedside. Do not use
  leukoreduction filters.
8. Quality Control Testing
  The following tests are recommended:
  8.1. Cell Counts: perform on final product to be infused.
  8.2. Cell Viability: perform on final product to be infused (Viable CD45+ determination by
  flow cytometric analysis recommended).
  8.3. Colony assay for CFU-GM, CFU-GEMM, and BFU-E: perform on final product to be
  infused.
  8.4. Viable CD34+ determination by flow cytometric analysis: perform on final product to
  be infused.
  8.5. Sterility test: perform on wash supernatant.
9. Emergency Product Recovery in Event of Primary Container Failure
  9.1 If the cryobag is compromised, move further handling into BSC after thawing.
  NOTE: It is the transplant physician’s (or designee’s) responsibility to determine
  whether the product will be used or discarded if the container is
  compromised at any step of the procedure.
  9.2 If the transplant physician (or designee) decides that the product should be used,
  recovery of the product may be attempted as described below.
  9.3 Use a long (3-5 inch) blunt needle (a sterile spinal needle with trochar removed if
  available).
  9.4 Attach the blunt needle to a sterile 60 mL syringe.
  9.5 Aspirate the product from the cryobag and inject into a sterile transfer bag.
  9.6 Continue to the wash step for the transferred product.
  9.7 Start and complete the wash process for the transferred product.
  9.8 Perform sterility test on a sample of the recovered wash product.
  NOTE: Alert the clinical team at the transplant center that the product could potentially
  be contaminated.
  9.9 Contact the MD Anderson Cord Blood Bank at 1-713-563-8000 or 713-794-1908 if
  during thawing, any portion of the product container appears to be damaged or
  compromised. Save the ruptured cryobag if possible. The Cord Blood Bank will
  provide further instructions for return of the container, if required for investigation.

Distributed by:
MD Anderson Cord Blood Bank
1841 Old Spanish Trail
Houston, TX 77054
713-563-8000
U.S. License # 2072

PACKAGE LABEL

Store/Ship:
-150C or colder
Product: S1393V00
Label Version:
L 082.033.002
MD Anderson
Cord Blood Bank
Houston, TX
CBB 173
Cryopreserved HPC, Cord Blood (Buffy Coat Enriched)
10% DMSO, 1% Dextran 40,
0.8% Hydroxyethyl starch
See Attached Documents

Collection
Date
0150910316
01 APR 2015 03:16
Properly identify intended Recipient and Product
Rx only.
A
Rh POSITIVE
FOR USE BY INTENDED
RECIPIENT ONLY
INTENDED RECIPIENT
Name: Doe, John
DOB: 12/25/1992
ID: 123-456-7
DO NOT IRRADIATE
DO NOT USE LEUKOREDUCTION FILTER
CRYOPRESERVED
HPC, CORD BLOOD
Buffy Coat Enriched
Approx. 25 ml
10% DMSO, 1% DEXTRAN 40,
0.8% Hydroxyethyl starch
Store at -150°C or colder
See package insert for full prescribing
information and instructions for preparation
Expiration
Date
01 APR 2025 03:0316
ADDITIONAL CBU IDENTIFIERS
NMDP ID: 9876-5432-1
Local ID: 012345
Collected and Processed By
MD Anderson Cord Blood Bank
1841 Old Spanish Trail, Houston, TX
US License: 2072
Label Version: L 082.027.002